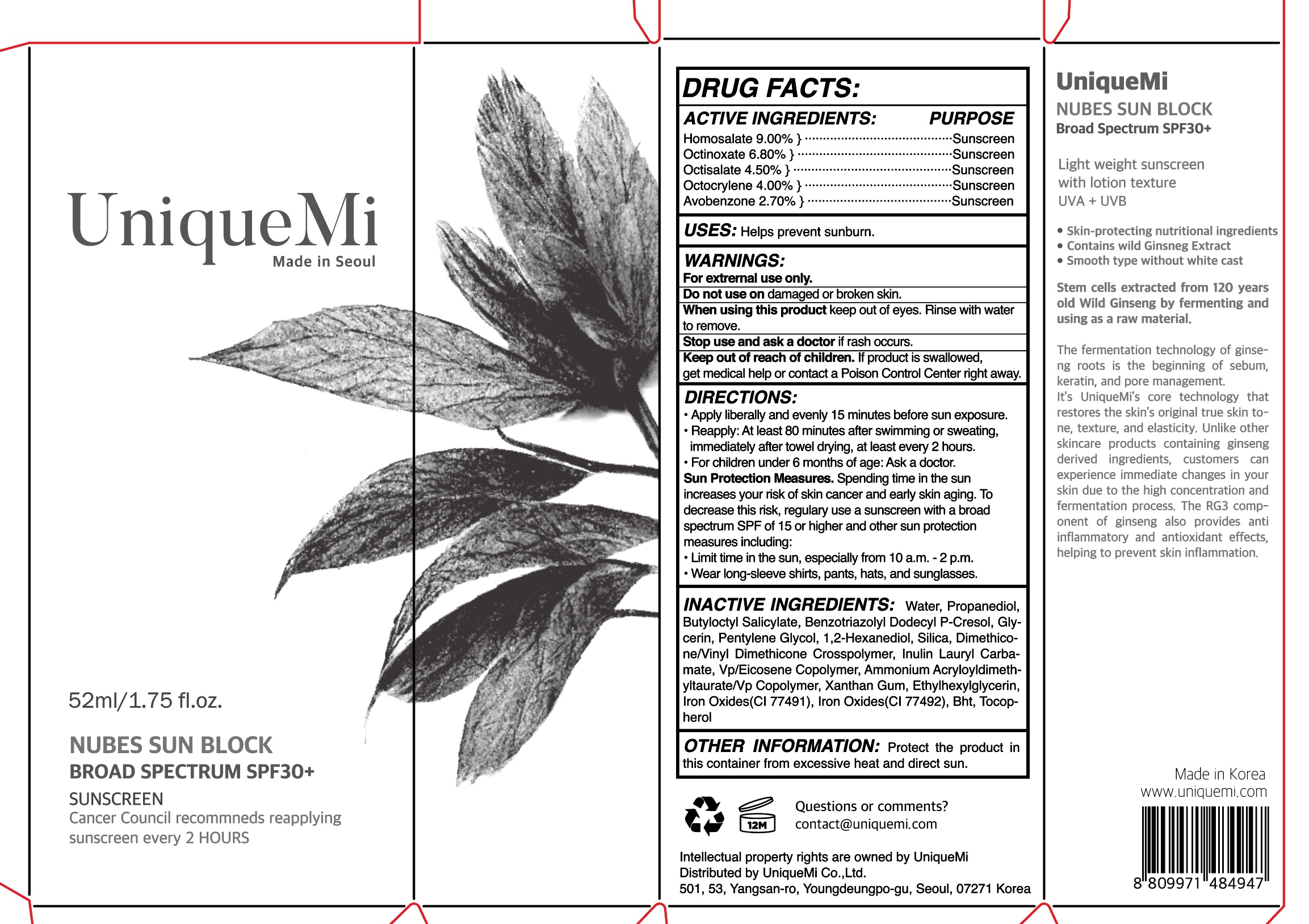 DRUG LABEL: Nubes SUN BLOCK
NDC: 84514-0001 | Form: CREAM
Manufacturer: UNIQUEMI
Category: otc | Type: HUMAN OTC DRUG LABEL
Date: 20240625

ACTIVE INGREDIENTS: HOMOSALATE 9 g/100 mL; OCTINOXATE 6.8 g/100 mL; OCTISALATE 4.5 g/100 mL; AVOBENZONE 2.7 g/100 mL; OCTOCRYLENE 4 g/100 mL
INACTIVE INGREDIENTS: WATER

Drug Facts

ACTIVE INGREDIENT

Homosalate 9.00% } ·········································Sunscreen

Octinoxate 6.80% } ···········································Sunscreen

Octisalate 4.50% } ············································Sunscreen

Octocrylene 4.00% } ·········································Sunscreen

Avobenzone 2.70% } ········································Sunscreen

INACTIVE INGREDIENT

Water, Propanediol, Butyloctyl Salicylate, Benzotriazolyl Dodecyl P-Cresol, Glycerin, Pentylene Glycol, 1,2-Hexanediol, Silica, Dimethicone/Vinyl Dimethicone Crosspolymer, Inulin Lauryl Carbamate, Vp/Eicosene Copolymer, Ammonium Acryloyldimethyltaurate/Vp Copolymer, Xanthan Gum, Ethylhexylglycerin,Iron Oxides(CI 77491), Iron Oxides(CI 77492), Bht, Tocophero

PURPOSE

helps prevent sunburn

keep out of reach of the children

INDICATIONS AND USAGE

• Apply liberally and evenly 15 minutes before sun exposure.

• Reapply: At least 80 minutes after swimming or sweating,

immediately after towel drying, at least every 2 hours.

• For children under 6 months of age: Ask a doctor.

Sun Protection Measures. Spending time in the sun

increases your risk of skin cancer and early skin aging. To

decrease this risk, regulary use a sunscreen with a broad

spectrum SPF of 15 or higher and other sun protection

measures including:

• Limit time in the sun, especially from 10 a.m. - 2 p.m.

• Wear long-sleeve shirts, pants, hats, and sunglasses.

WARNINGS

For extrernal use only.

Do not use on damaged or broken skin.

When using this product keep out of eyes. Rinse with water

to remove.

Stop use and ask a doctor if rash occurs.

Keep out of reach of children. If product is swallowed,

get medical help or contact a Poison Control Center right away.

DOSAGE AND ADMINISTRATION

topical use only